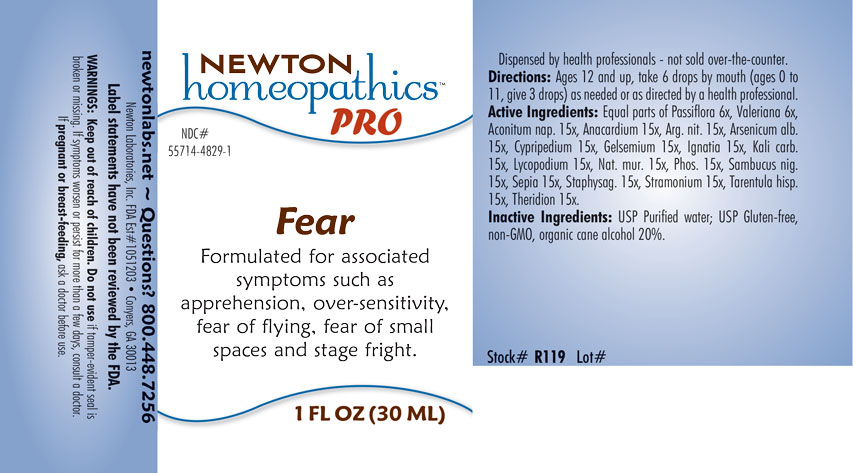 DRUG LABEL: Fear
NDC: 55714-4829 | Form: LIQUID
Manufacturer: Newton Laboratories, Inc.
Category: homeopathic | Type: HUMAN OTC DRUG LABEL
Date: 20201203

ACTIVE INGREDIENTS: ACONITUM NAPELLUS 15 [hp_X]/1 mL; SEMECARPUS ANACARDIUM JUICE 15 [hp_X]/1 mL; SILVER NITRATE 15 [hp_X]/1 mL; ARSENIC TRIOXIDE 15 [hp_X]/1 mL; CYPRIPEDIUM PARVIFLORUM VAR. PUBESCENS ROOT 15 [hp_X]/1 mL; GELSEMIUM SEMPERVIRENS ROOT 15 [hp_X]/1 mL; STRYCHNOS IGNATII SEED 15 [hp_X]/1 mL; POTASSIUM CARBONATE 15 [hp_X]/1 mL; LYCOPODIUM CLAVATUM SPORE 15 [hp_X]/1 mL; SODIUM CHLORIDE 15 [hp_X]/1 mL; PHOSPHORUS 15 [hp_X]/1 mL; SAMBUCUS NIGRA FLOWERING TOP 15 [hp_X]/1 mL; SEPIA OFFICINALIS JUICE 15 [hp_X]/1 mL; DELPHINIUM STAPHISAGRIA SEED 15 [hp_X]/1 mL; DATURA STRAMONIUM 15 [hp_X]/1 mL; LYCOSA TARANTULA 15 [hp_X]/1 mL; THERIDION CURASSAVICUM 15 [hp_X]/1 mL; PASSIFLORA INCARNATA FLOWERING TOP 6 [hp_X]/1 mL; VALERIAN 6 [hp_X]/1 mL
INACTIVE INGREDIENTS: ALCOHOL; WATER

Fear 4829L

INDICATIONS & USAGE SECTION

Formulated for associated symptoms such as apprehension, over-sensitivity, fear of flying, fear of small places and stage fright.

DOSAGE & ADMINISTRATION SECTION

Directions: Ages 12 and up, take 6 drops by mouth (ages 0 to 11, give 3 drops) as needed or as directed by a health professional.

OTC - ACTIVE INGREDIENT SECTION

Active Ingredients: Equal parts of Passiflora incarnata 6x, Valeriana officinalis 6x, Aconitum napellus 15x, Anacardium orientale 15x, Argentum nitricum 15x, Arsenicum album 15x, Cypripedium pubescens 15x, Gelsemium sempervirens 15x, Ignatia amara 15x, Kali carbonicum 15x, Lycopodium clavatum 15x, Natrum muriaticum 15x, Phosphorus 15x, Sambucus nigra 15x, Sepia 15x, Staphysagria 15x, Stramonium 15x, Tarentula hispana 15x, Theridion 15x

OTC - PURPOSE SECTION

Formulated for associated symptoms such as apprehension, over-sensitivity, fear of flying, fear of small spaces and stage fright.

INACTIVE INGREDIENT SECTION

Inactive Ingredients: USP Purified Water; USP Gluten-free, non-GMO, organic cane alcohol 20%.

QUESTIONS SECTION

newtonlabs.net – Questions? 800.448.7256

Newton Laboratories, Inc. FDA Est # 1051203 - Conyers, GA 30013

WARNINGS SECTION

WARNINGS: Keep out of reach of children. Do not use if tamper-evident seal is broken or missing. If symptoms worsen or persist for more than a few days, consult a doctor. If pregnant or breast-feeding, ask a doctor before use.

OTC - PREGNANCY OR BREAST FEEDING SECTION

If pregnant or breast-feeding, ask a doctor before use.

OTC - KEEP OUT OF REACH OF CHILDREN SECTION

Keep out of reach of children.